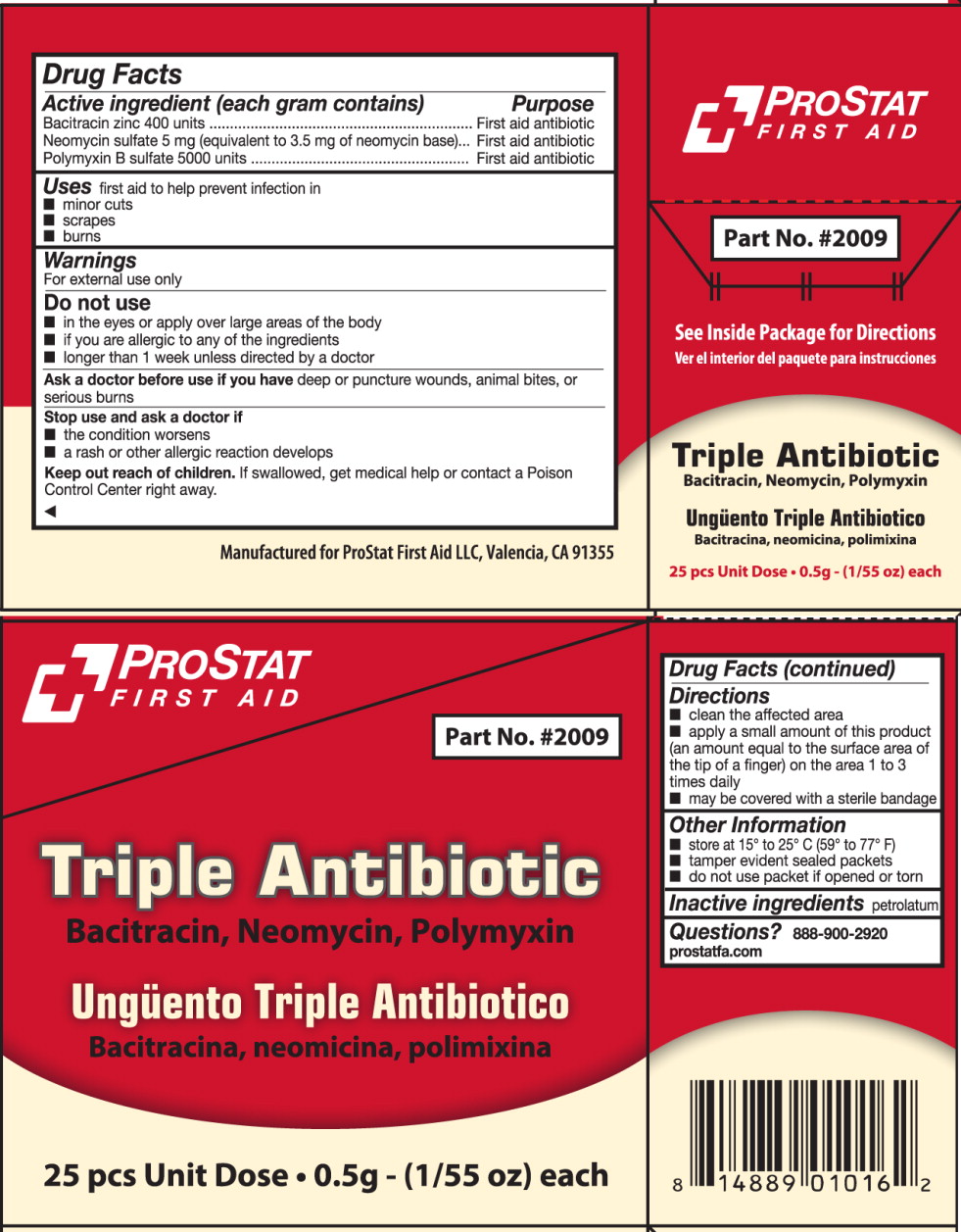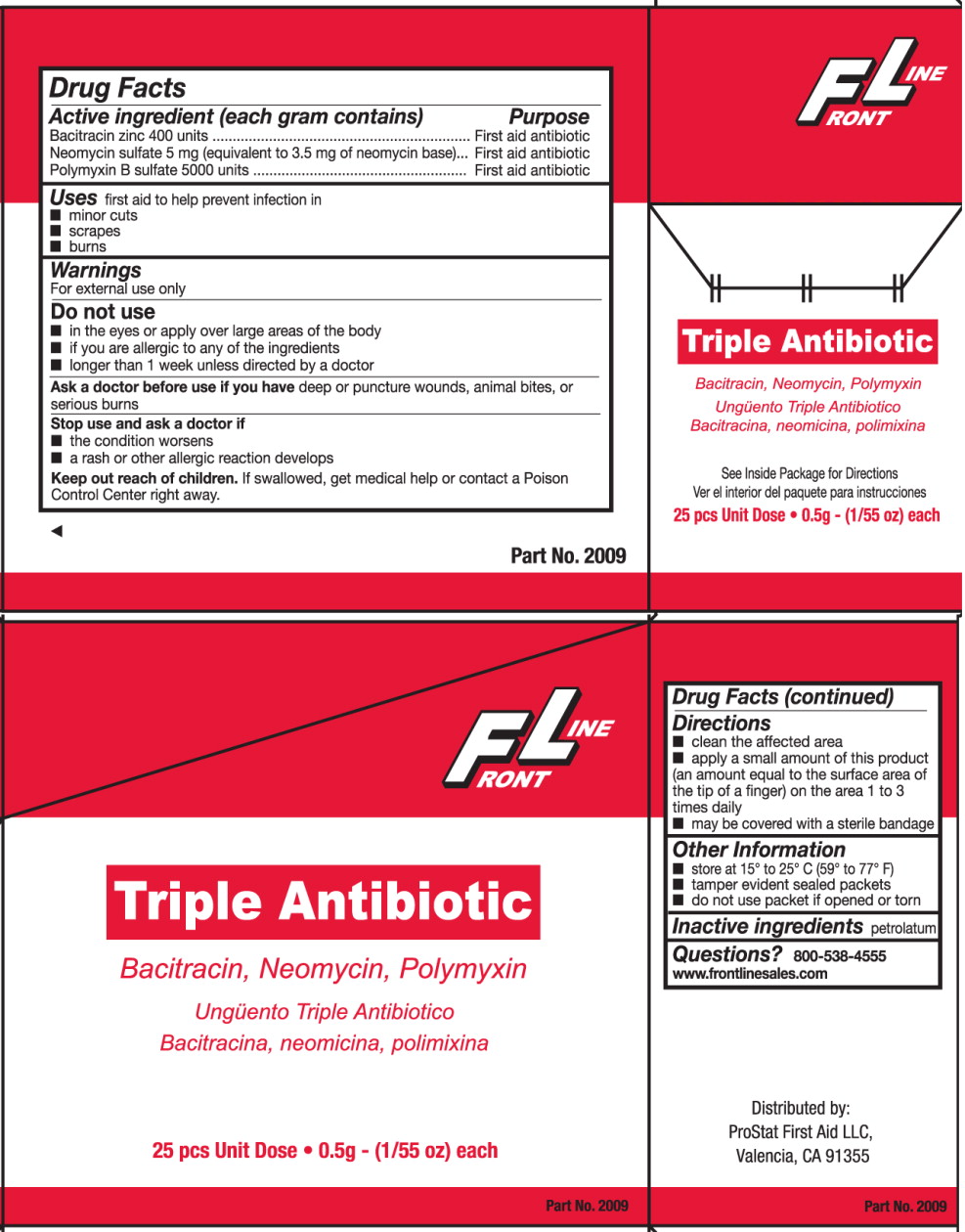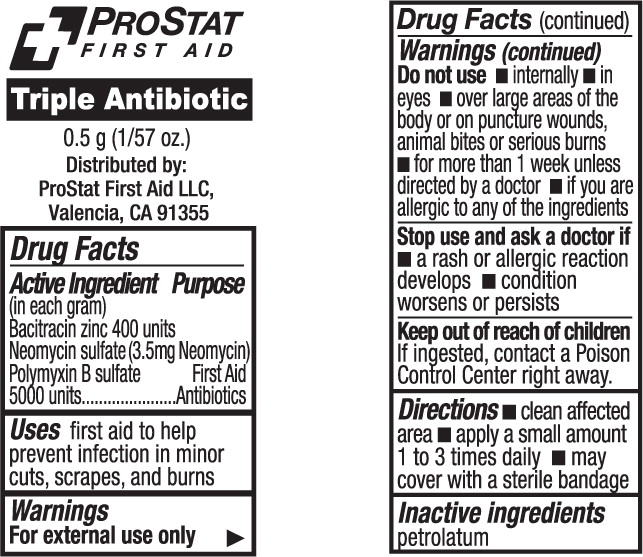 DRUG LABEL: Triple Antibiotic
NDC: 58228-5600 | Form: OINTMENT
Manufacturer: ProStat First Aid
Category: otc | Type: HUMAN OTC DRUG LABEL
Date: 20130920

ACTIVE INGREDIENTS: bacitracin zinc 400 [USP'U]/1 g; neomycin sulfate 3.5 mg/1 g; polymyxin b sulfate 5000 [USP'U]/1 g
INACTIVE INGREDIENTS: petrolatum

Drug Facts

Active Ingredients (each gram contains)

Bacitracin zinc 400 units

Neomycin sulfate 5 mg
(equivalent to 3.5 mg of neomycin base)

Polymyxin B sulfate 5000 units

Purpose

First Aid Antibiotic

Uses

first aid to help prevent infection in:

- minor cuts
- scrapes
- burns

Warnings

For external use only

Do not use:

- in the eyes or apply over large areas of the body
- if you are allergic to any of the ingredients
- longer than 1 week unless directed by a doctor

Ask a doctor before use if you have deep or puncture wounds, animal bites, or serious burns

Stop use and ask a doctor if

- the condition worsens
- a rash or other allergic reaction develops

Keep out of reach of children. If swallowed, get medical help or contact a Poison Control Center right away.

Directions

- clean the affected area
- apply a small amount of this product (an amount equal to the surface area of the tip of a finger) on the area 1 to 3 times daily
- may be covered with a sterile bandage

Other Information

- store at 15°-25°C (59°-77°F)
- tamper evident sealed packets
- do not use packet if opened or torn

Inactive ingredients

petrolatum

Questions?

888.900.2920

prostatfa.com

PRINCIPAL DISPLAY PANEL – ProStat 25 count box

PROSTAT
FIRST AID

Part No. #2009

Triple Antibiotic
Bacitracin, Neomycin, Polymyxin

Ungüento Triple Antibiotico
Bacitracina, neomicina, polimixina

25 pcs Unit Dose • 0.5g - (1/55 oz) each

PRINCIPAL DISPLAY PANEL – Front Line 25 count box

FRONT LINE

Triple Antibiotic
Bacitracin, Neomycin, Polymyxin

Ungüento Triple Antibiotico
Bacitracina, neomicina, polimixina

25 pcs Unit Dose • 0.5g - (1/55 oz) each

PRINCIPAL DISPLAY PANEL – packet

PROSTAT
FIRST AID

Triple Antibiotic
0.5 g (1/57oz)

Distributed by:
ProStat First Aid LLC,
Valencia, CA 91355